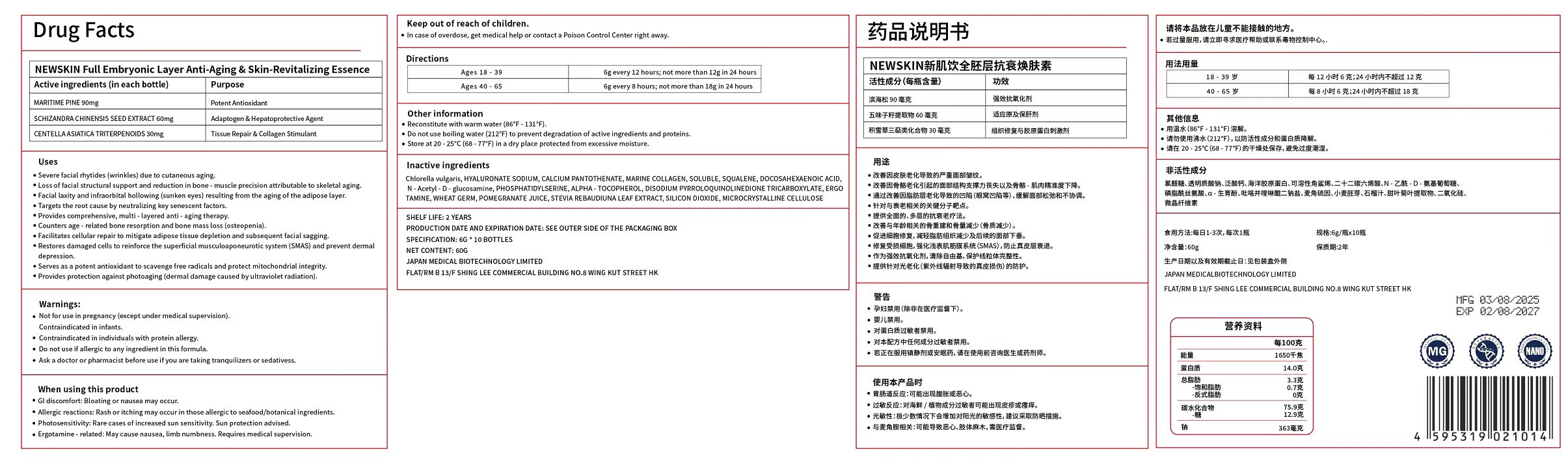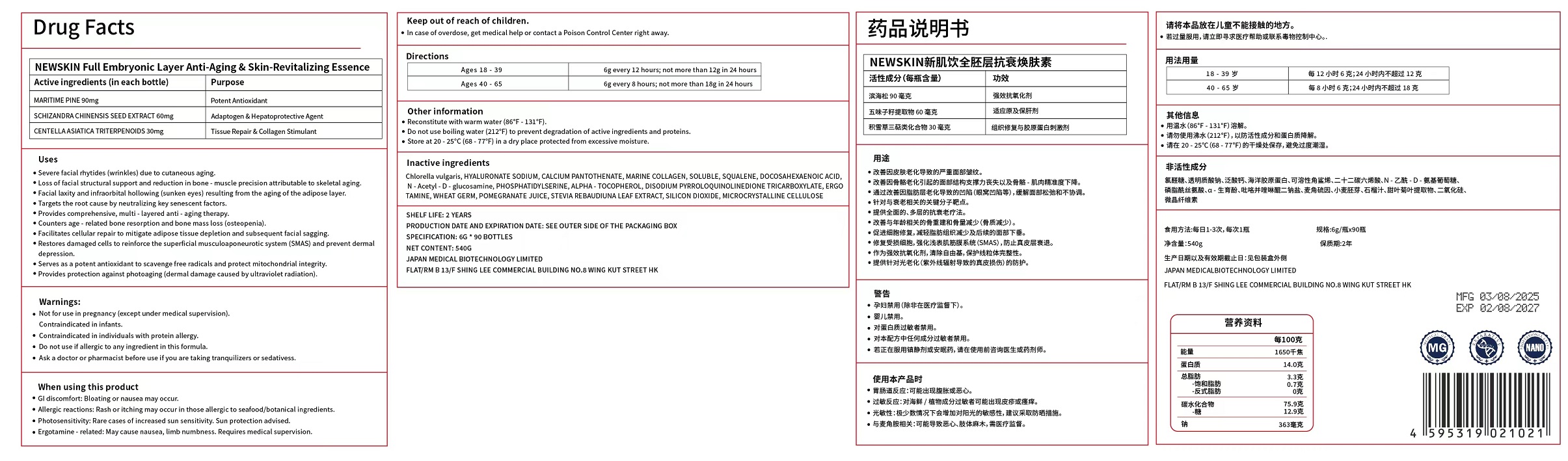 DRUG LABEL: NEWSKIN  Whole Embryonic Layer Anti-Aging Skin Renewal Powde
NDC: 87130-002 | Form: POWDER
Manufacturer: Japan Medical Biotechnology Limited
Category: otc | Type: HUMAN OTC DRUG LABEL
Date: 20260113

ACTIVE INGREDIENTS: CENTELLA ASIATICA TRITERPENOIDS 30 mg/6 g; MARITIME PINE 90 mg/6 g; SCHISANDRA CHINENSIS SEED 60 mg/6 g
INACTIVE INGREDIENTS: DISODIUM PYRROLOQUINOLINEDIONE TRICARBOXYLATE; WHEAT GERM; STEVIA REBAUDIUNA LEAF; CALCIUM PANTOTHENATE; MICROCRYSTALLINE CELLULOSE; PHOSPHATIDYLSERINE; HYALURONATE SODIUM; MARINE COLLAGEN, SOLUBLE; POMEGRANATE JUICE; .ALPHA.-TOCOPHEROL; SQUALENE; SILICON DIOXIDE; CHLORELLA VULGARIS; DOCOSAHEXAENOIC ACID; ERGOTAMINE; N-ACETYLGLUCOSAMINE

87130-002

Active ingredient（in each tablet）

MARITIME PINE 90mg

SCHIZANDRA CHINENSIS SEED EXTRACT 60mg

CENTELLA ASIATICA TRITERPENOIDS 30mg

Purpose

Potent Antioxidant

Adaptogen & Hepatoprotective Agent

Tissue Repair & Collagen Stimulant

Uses

Severe facial rhytides (wrinkles) due to cutaneous aging.
Loss of facial structural support and reduction in bone-muscle precision attributable to skeletal aging.

Facial laxity and infraorbital hollowing (sunken eyes) resulting from the aging of the adipose layer.

Targets the root cause by neutralizing key senescent factors.
Provides comprehensive, multi-layered anti-aging therapy.
Counters age-related bone resorption and bone mass loss (osteopenia).
Facilitates cellular repair to mitigate adipose tissue depletion and subsequent facial sagging.
Restores damaged cells to reinforce the superficial musculoaponeurotic system (SMAS) and prevent dermal depression.
Serves as a potent antioxidant to scavenge free radicals and protect mitochondrial integrity.
Provides protection against photoaging (dermal damage caused by ultraviolet radiation).

Warnings

Not for use in pregnancy (except under medical supervision).
Contraindicated in infants.
Contraindicated in individuals with protein allergy.

Do not use if allergic to any ingredient in this formula.

Ask a doctor or pharmacist before use if

you are taking tranquilizers or sedatives

When using this product

GI discomfort: Bloating or nausea may occur.
Allergic reactions: Rash or itching may occur in those allergic to seafood/botanical ingredients.
Photosensitivity: Rare cases of increased sun sensitivity. Sun protection advised.

Ergotamine-related: May cause nausea, limb numbness. Requires medical supervision.

Keep out of reach of children.

In case of overdose,get medical help or contact a Poison Control Center right away.

Directions

Ages 18-39: 6g every 12 hours; not more than 12g in 24hours

Ages 40-65: 6g every 8 hours; not more than 18g in 24hours

Other information

Reconstitute with warm water (86°F-131°F).

Do not use boiling water (212°F) to prevent degradation of active ingredients and proteins.

Store at 20-25°C (68-77°F) in a dry place protected from excessive moisture.

Inactive ingredients

Chlorella vulgaris, HYALURONATE SODIUM, CALCIUM PANTOTHENATE, MARINE COLLAGEN, SOLUBLE, SQUALENE, DOCOSAHEXAENOIC ACID, N-Acetyl-D-glucosamine, PHOSPHATIDYLSERINE, .ALPHA.-TOCOPHEROL, DISODIUM PYRROLOQUINOLINEDIONE TRICARBOXYLATE, ERGOTAMINE, WHEAT GERM, POMEGRANATE JUICE, STEVIA REBAUDIUNA LEAF EXTRACT, SILICON DIOXIDE, MICROCRYSTALLINE CELLULOSE